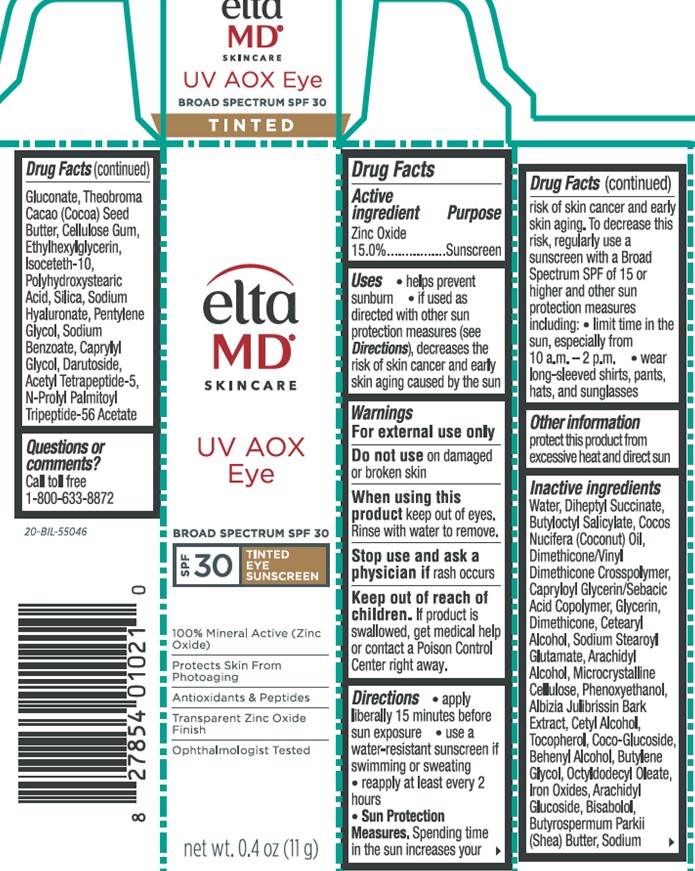 DRUG LABEL: Elta MD UV AOX Eye
NDC: 72043-4342 | Form: CREAM
Manufacturer: CP Skin Health Group, Inc.
Category: otc | Type: HUMAN OTC DRUG LABEL
Date: 20240131

ACTIVE INGREDIENTS: ZINC OXIDE 15 g/100 g
INACTIVE INGREDIENTS: WATER

Elta MD UV AOX Eye

Directions

Apply liberally 15 minutes before sun exposure

Use a water resistent sunscreen if swimming or sweating

Reapply at least every 2 hours

Warning

For external use only

Do not use on damaged or broken skin

When using this product keep out of eye. Rinse with water to remove.

Stop use and ask a physician if rash occurs

INACTIVE INGREDIENT

Water, Diheptul Succinate, Butyloctyl Salicylate, Cocos Nucifera (Coconut) Oil, Dimethicone Crosspolymer, Capryloyl Glycerin/Sebacic Acid Copolymer, Glycerin, Dimethicone, Cetearyl Alcohol, Sodium Stearoyl Glutamate, Arachidyl Alcohol, Microcrystalline Cellulose, Phenoxyethanol, Albizia Julibrissin Bark Extract, Cetyl Alcohol, Tocopherol, Coco-Glucoside, Behenyl Alcohol, Butylene Glycol, Octyldodecyl Oleate, Iron Oxides, Arachidyl Glucoside, Bisabolol, Butyrospermum Parkaii (Shea) Butter, Sodium Gluconate, Theobroma Cacao (Cocoa) Seed Butter, Cellulose Gum, Ethylhexylglycerin, Isoceteth-10, Polyhydrocxystearic Acid, Silica, Sodium Hyaluronate, Pentylene, Glycol, Sodium Benzoate, Carprylyl Glycol, Darutoside, Acetyl Tetrapeptide-5, N-Prolyl Palmitoyl Tripeptide-56 Acetate

Uses

Helps prevent sunburn

If used as directed with other sun protection measures (see Directions), decreases the risk of skin cancer and early skin aging caused by the sun

Keep out of reach of children

If product is swallowed, get medical help or contact a Poison Control Center right away.

Purpose

Sunscreen